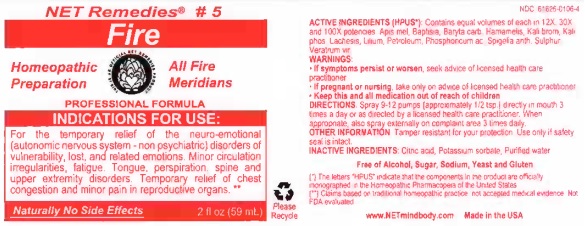 DRUG LABEL: Fire
NDC: 61626-0106 | Form: LIQUID
Manufacturer: NET Remedies
Category: homeopathic | Type: HUMAN PRESCRIPTION DRUG LABEL
Date: 20210119

ACTIVE INGREDIENTS: APIS MELLIFERA 12 [hp_X]/59 mL; BAPTISIA TINCTORIA ROOT 12 [hp_X]/59 mL; BARIUM CARBONATE 12 [hp_X]/59 mL; HAMAMELIS VIRGINIANA ROOT BARK/STEM BARK 12 [hp_X]/59 mL; POTASSIUM BROMIDE 12 [hp_X]/59 mL; DIBASIC POTASSIUM PHOSPHATE 12 [hp_X]/59 mL; LACHESIS MUTA VENOM 12 [hp_X]/59 mL; LILIUM LANCIFOLIUM BULB 12 [hp_X]/59 mL; KEROSENE 12 [hp_X]/59 mL; PHOSPHORIC ACID 12 [hp_X]/59 mL; SPIGELIA ANTHELMIA 12 [hp_X]/59 mL; SULFUR 12 [hp_X]/59 mL; VERATRUM VIRIDE ROOT 12 [hp_X]/59 mL
INACTIVE INGREDIENTS: CITRIC ACID MONOHYDRATE; POTASSIUM SORBATE; WATER

Fire

ACTIVE INGREDIENT

ACTIVE INGREDIENTS (HPUS*): Contains equal volumes of each in 12X, 30X, and 100X potencies: Apis mel, Baptisia, Baryta carb, Hamamelis, Kali brom, Kali phos, Lachesis, Lilium, Petroleum, Phosphoricum ac, Spigelia anth, Sulphur, Veratrum vir.

(*) The letters "HPUS" indicate that the components in the product are officially monographed in the Homeopathic Pharmacopoeia of the United States.

(**) Claims based on traditional homeopathic practice, not accepted medical evidence. Not FDA evaluated.

INDICATIONS AND USAGE

INDICATIONS FOR USE: For temporary relief of the neuro-emotional (autonomic nervous system - non psychiatric) disorders of vulnerability, lost, and related emotions. Minor circulation irregularities, fatigue. Tongue, perspiration, spine, and upper extremity disorders. Temporary relief of chest congestion and minor pain in reproductive organs.**

WARNINGS:

• If symptoms persist or worsen, seek advice of licensed health care practicioner.
• If pregnant or nursing, take only advice of licensed health care practitioner.
• Keep this and all medication out of reach of children.

KEEP OUT OF REACH OF CHILDREN

• Keep this and all medication out of reach of children.

DOSAGE AND ADMINISTRATION

DIRECTIONS: Spray 9-12 pumps (approximately 1/2 tsp.) directly in mouth 3 times a day or as directed by a licensed health care practicioner. When appropriate, also spray externally on complaint area 3 times daily.

OTHER INFORMATION:

Tamper resistant for your protection. Use only if safety seal is intact.

INACTIVE INGREDIENTS: Citric acid, Potassium sorbate, Purified water.

Free of Alcohol, Sugar, Sodium, Yeast and Gluten.

QUESTIONS

www.NETmindbody.com

Made in the USA

PACKAGE LABEL

NET Remedies #5

Fire

Homeopathic

Preparation

All Fire Meridians

PROFESSIONAL FORMULA

Naturally No Side Effects

2 fl oz (59 mL)

PURPOSE

For temporary relief of the neuro-emotional (autonomic nervous system - non psychiatric) disorders of vulnerability, lost, and related emotions. Minor circulation irregularities, fatigue. Tongue, perspiration, spine, and upper extremity disorders. Temporary relief of chest congestion and minor pain in reproductive organs.**